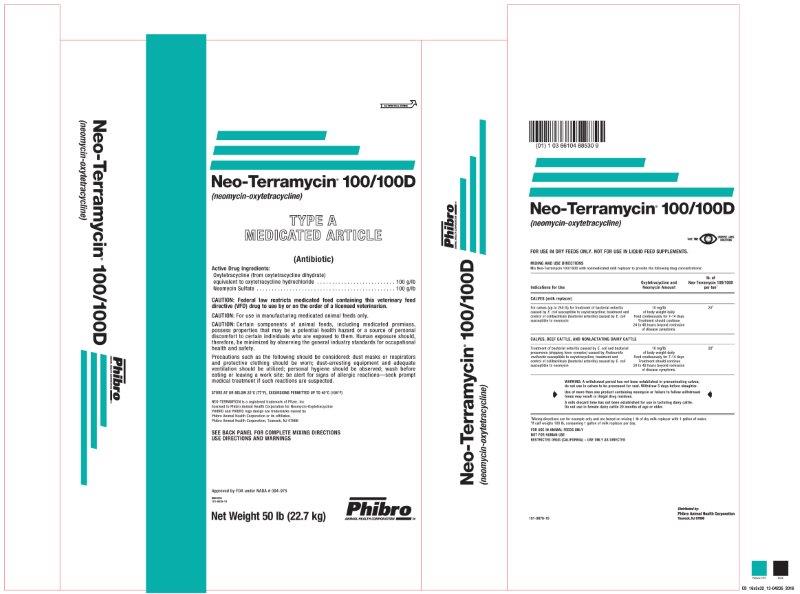 DRUG LABEL: Neo-Terramycin 100/100D
NDC: 66104-8853 | Form: POWDER
Manufacturer: Phibro Animal Health
Category: animal | Type: VFD TYPE A MEDICATED ARTICLE ANIMAL DRUG LABEL
Date: 20260121

ACTIVE INGREDIENTS: OXYTETRACYCLINE HYDROCHLORIDE 100 g/0.45 kg; NEOMYCIN SULFATE 100 g/0.45 kg
INACTIVE INGREDIENTS: MINERAL OIL; SODIUM ALUMINOSILICATE; SUCROSE

Neo-Terramycin® 100/100D
(neomycin-oxytetracycline)
TYPE A MEDICATED ARTICLE

Active Drug Ingredients:

Oxytetracycline (from oxytetracycline dihydrate)

equivalent to oxytetracycline hydrochloride . . . . . . . . . . . . . . . . . . . . . . . . . 100 g/lb

Neomycin Sulfate . . . . . . . . . . . . . . . . . . . . . . . . . . . . . . . . . . . . . . . . . . . . . . 100 g/lb

CAUTION:

CAUTION: Federal law restricts medicated feed containing this veterinary feed directive (VFD) drug to use by or on the order of a licensed veterinarian.

CAUTION: For use in manufacturing medicated animal feeds only.

CAUTION: Certain components of animal feeds, including medicated premixes, possess properties that may be a potential health hazard or a source of personal discomfort to certain individuals who are exposed to them. Human exposure should, therefore, be minimized by observing the general industry standards for occupational health and safety.

Precautions such as the following should be considered: dust masks or respirators and protective clothing should be worn; dust-arresting equipment and adequate ventilation should be utilized; personal hygiene should be observed; wash before eating or leaving a work site; be alert for signs of allergic reactions—seek prompt medical treatment if such reactions are suspected.

STORE IN A DRY, COOL PLACE

STORE AT OR BELOW 25°C (77°F), EXCURSIONS PERMITTED UP TO 40°C (104°F)

NEO-TERRAMYCIN is a registered trademark of Pfizer, Inc

licensed to Phibro Animal Health Corporation for Neomycin-Oxytetracycline

PHIBRO and PHIBRO logo design are trademarks owned by

Phibro Animal Health Corporation of its affiliates.

Phibro Animal Health Corporation, Teaneck, NJ 07666

MIXING AND USE DIRECTIONS

Mix Neo-Terramycin 100/100D with nonmedicated milk replacer to provide the following drug concentrations:

Indications for Use | Oxytetracycline and; Neomycin Amount | lb. of; Neo-Terramycin 100/100D per ton^1
CALVES (milk replacer)
For calves (up to 250 lb) for treatment of bacterial enteritis caused by E. coli susceptible to oxytetracycline; treatment and control of colibacillosis (bacterial enteritis) caused by E. coli susceptible to neomycin | 10 mg/lb of body weight daily; Feed continuously for 7-14 days; Treatment should continue 24 to 48 hours beyond remission of disease symptoms. | 20^2
CALVES, BEEF CATTLE, AND NONLACTATING DAIRY CATTLE
Treatment of bacterial enteritis caused by E. coli and bacterial pneumonia (shipping fever complex) caused by Pasteurella multocida susceptible to oxytetracycline; treatment and control of colibacillosis (bacterial enteritis) caused by E. coli susceptible to neomycin | 10 mg/lb of body weight daily; Feed continuously for 7-14 days; Treatment should continue 24 to 48 hours beyond remission of disease symptoms. | 20^2
WARNING: A withdrawal period has not been established in preruminating calves; do not use in calves to be processed for veal. At the 10 mg/lb level, withdraw 5 days before slaughter.
Use of more than one product containing neomycin or failure to follow withdrawal times may result in illegal drug residues.
A milk discard time has not been established for use in lactating dairy cattle.
Do not use in female dairy cattle 20 months of age or older.
^1Mixing directions are for example only and are based on mixing 1 lb of dry milk replacer with 1 gallon of water.
^2If calf weighs 100 lb, consuming 1 gallon of milk replacer per day.

INDICATIONS AND USAGE

FOR USE IN ANIMAL FEEDS ONLY

NOT FOR HUMAN USE

RESTRICTED DRUG (CALIFORNIA) – USE ONLY AS DIRECTED

Neo-Terramycin 100-100D Label